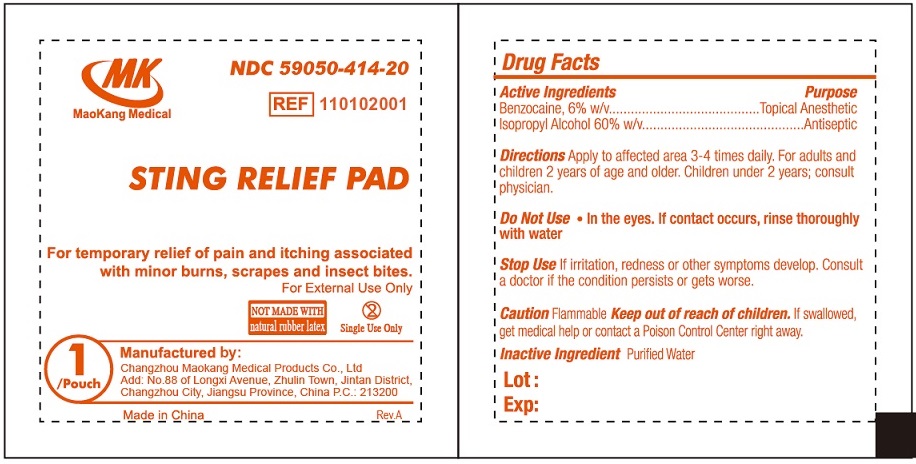 DRUG LABEL: MK Sting Relief Pads
NDC: 59050-414 | Form: LIQUID
Manufacturer: Changzhou Maokang Medical Products Co., Ltd
Category: otc | Type: HUMAN OTC DRUG LABEL
Date: 20231109

ACTIVE INGREDIENTS: BENZOCAINE 60 mg/1 mL; ISOPROPYL ALCOHOL 600 mg/1 mL
INACTIVE INGREDIENTS: WATER

MK Sting Relief Pads

Active ingredients

Benzocaine 6.0% w/v

Isopropyl Alcohol 60% w/v

Purpose

Topical Anesthetic

Antiseptic

Directions

Apply to affected area 3-4 times daily. For adults and children 2 years of age and older. Children under 2 years; consult physician.

INDICATIONS AND USAGE

- For temporary relief of pain and itching associated with minor burns, scrapes and insect bites.

Warnings

For external use only.

Flammable Caution

Do Not Use

- in the eyes. If contact occurs, rinse thoroughly with water

Stop Use

If irritation, redness or other symptoms develop. Consult a doctor if the condition persists or gets worse.

Keep out of reach of children.

If swallowed, get medical help or contact a Poison Control center right away.

Inactive ingredients:

Purified Water